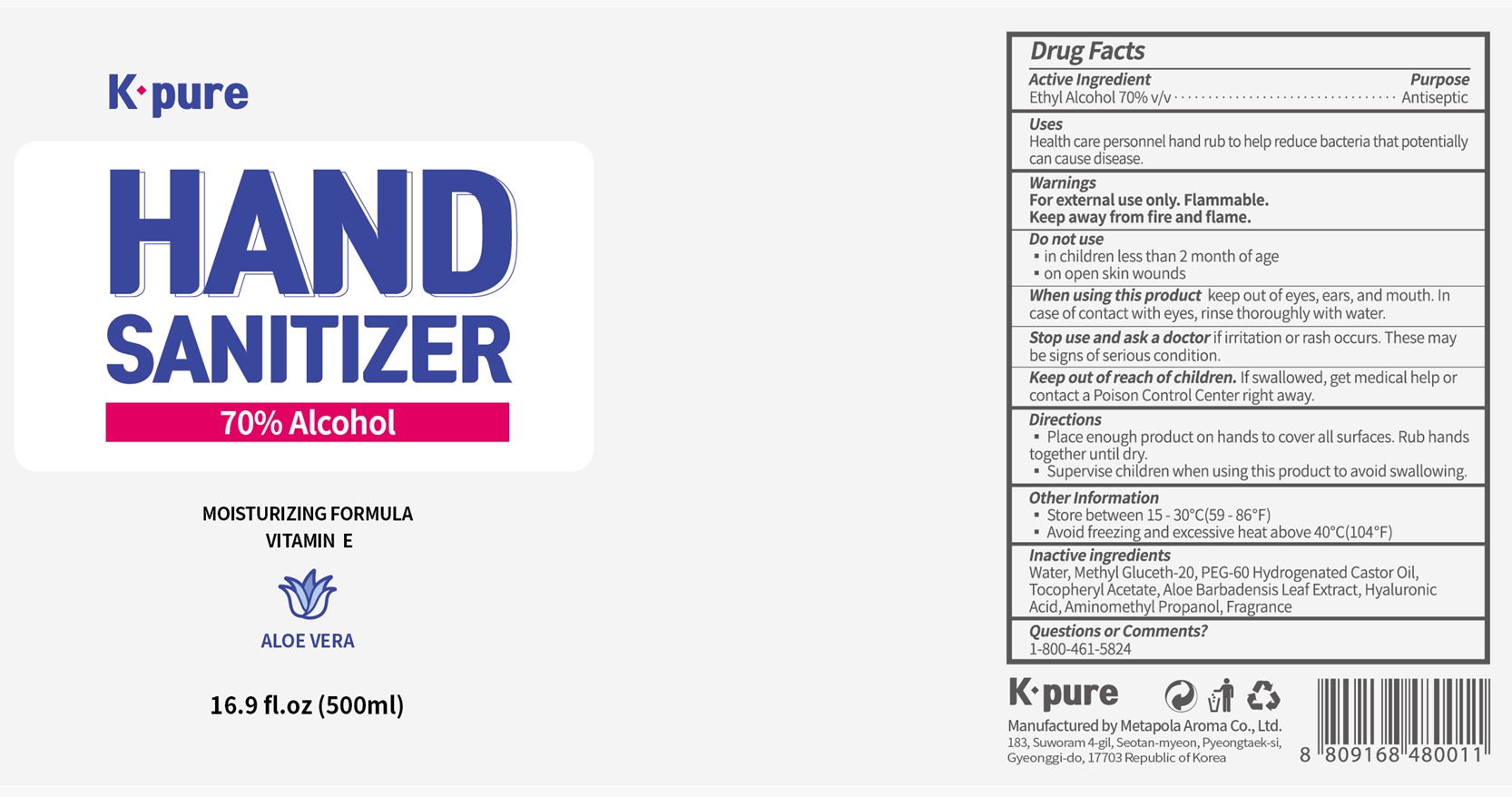 DRUG LABEL: K-pure Hand Sanitizer 70% 500ml
NDC: 77680-100 | Form: GEL
Manufacturer: Metapola Aroma Co., Ltd.
Category: otc | Type: HUMAN OTC DRUG LABEL
Date: 20200714

ACTIVE INGREDIENTS: ALCOHOL 70 mL/100 mL
INACTIVE INGREDIENTS: ALOE VERA LEAF; WATER; HYALURONIC ACID; PEG-60 HYDROGENATED CASTOR OIL; ALPHA-TOCOPHEROL ACETATE; AMINOMETHYLPROPANOL; METHYL GLUCETH-20

Kpure Hand Sanitizer 70% 500ml

Active Ingredient(s)

Ethyl Alcohol 70% v/v

Purpose

Antiseptic

Use

Health care personnel hand rub to help reduce bacteria that potentially can cause disease.

Warnings

For external use only. Flammable. Keep away from heat or flame

Do not use

- in children less than 2 months of age
- on open skin wounds

When using this product keep out of eyes, ears, and mouth. In case of contact with eyes, rinse eyes thoroughly with water.

Stop use and ask a doctor if irritation or rash occurs. These may be signs of a serious condition.

Keep out of reach of children. If swallowed, get medical help or contact a Poison Control Center right away.

Directions

- Place enough product on hands to cover all surfaces. Rub hands together until dry.
- Supervise children under 6 years of age when using this product to avoid swallowing.

Other information

- Store between 15-30C (59-86F)
- Avoid freezing and excessive heat above 40C (104F)

Inactive ingredients

Water, Methyl Gluceth-20, PEG-60 Hydrogenated Castor Oil, Tocopheryl Acetate, Aloe Barbadensis Leaf Extract, Hyaluronic Acid, Aminomethyl Propanol, Fragrance

Questions or Comments?

1-800-461-5824

Package Label - Principal Display Panel

K-Pure

HAND

SANITIZER

70% Alcohol

MOISTURIZING FORMULA

VITAMIN E

ALOE VERA

16.9 fl.oz (500ml)